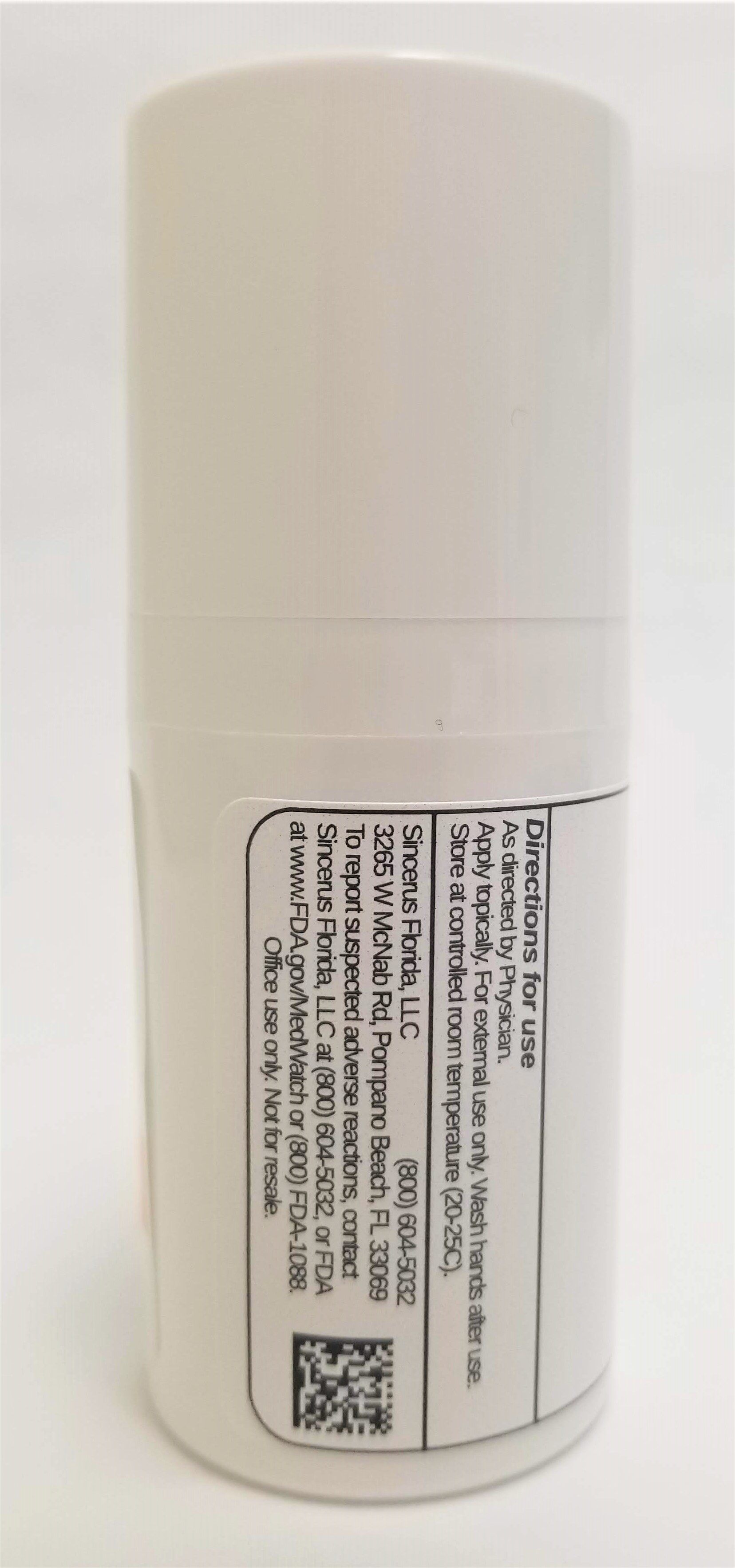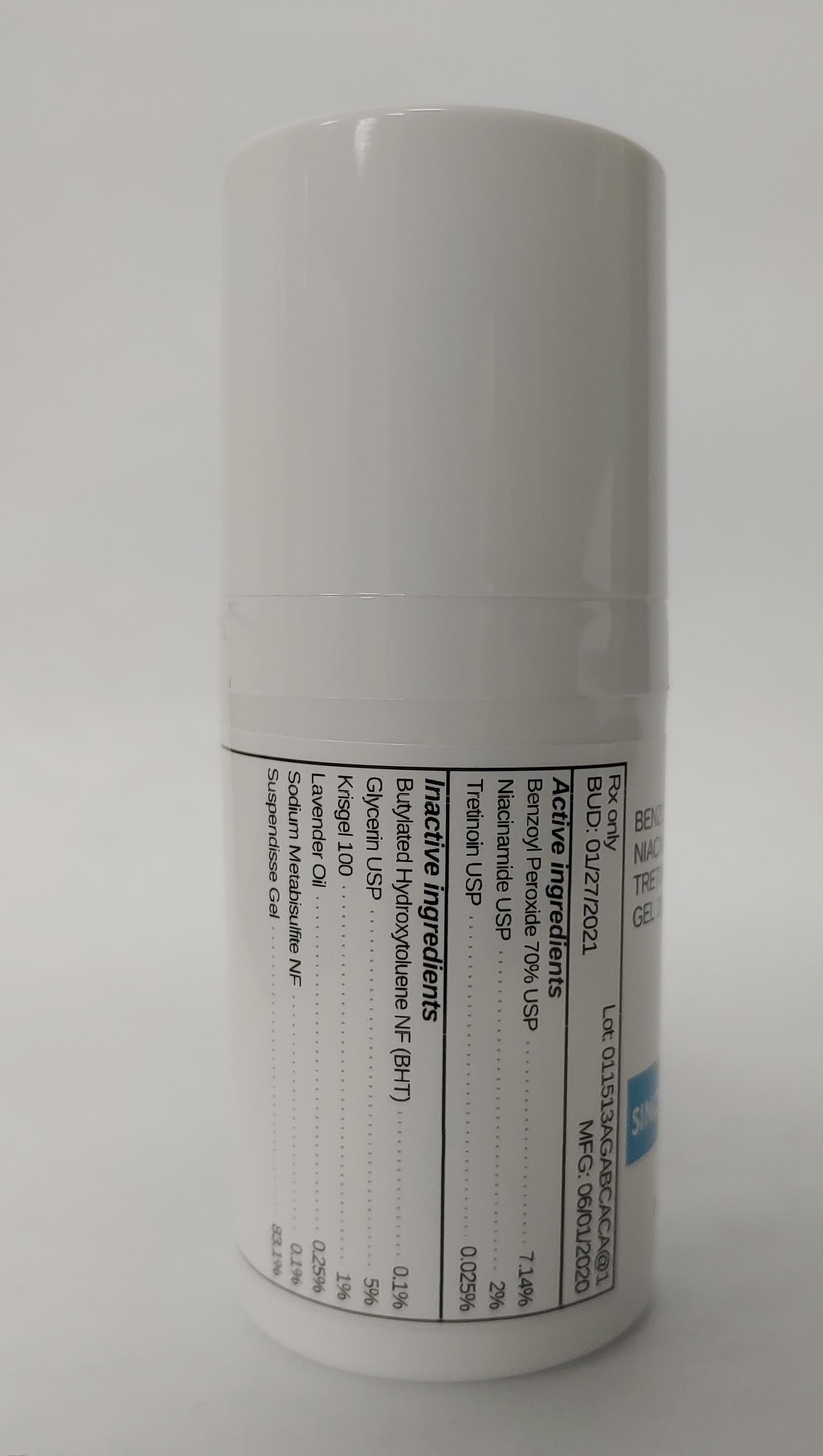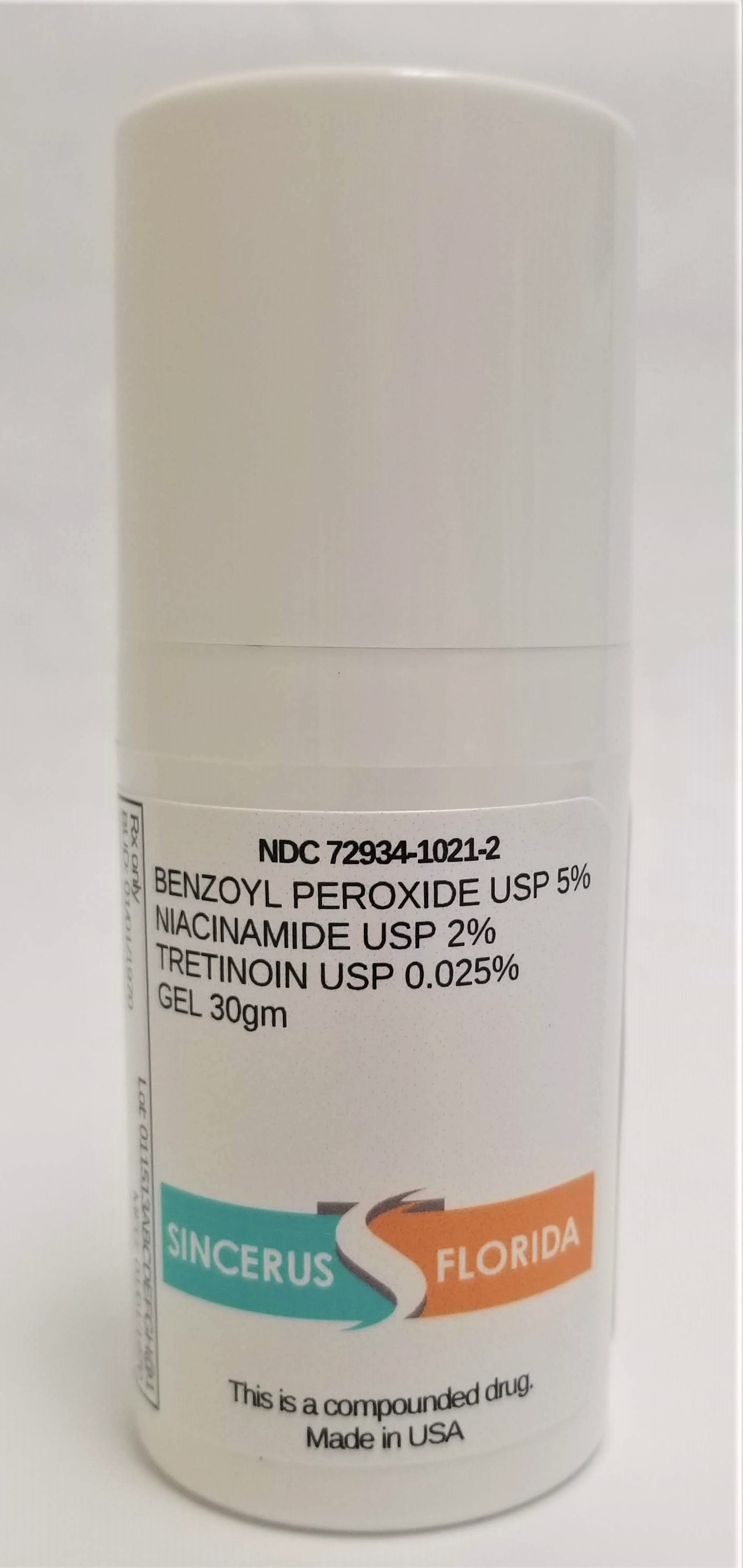 DRUG LABEL: BENZOYL PEROXIDE 5% / NIACINAMIDE 2% / TRETINOIN 0.025%
NDC: 72934-1021 | Form: GEL
Manufacturer: Sincerus, Florida, LLC
Category: prescription | Type: HUMAN PRESCRIPTION DRUG LABEL
Date: 20200603

ACTIVE INGREDIENTS: BENZOYL PEROXIDE 5 g/100 g; NIACINAMIDE 2 g/100 g; TRETINOIN 0.025 g/100 g

BENZOYL PEROXIDE 5% / NIACINAMIDE 2% / TRETINOIN 0.025%